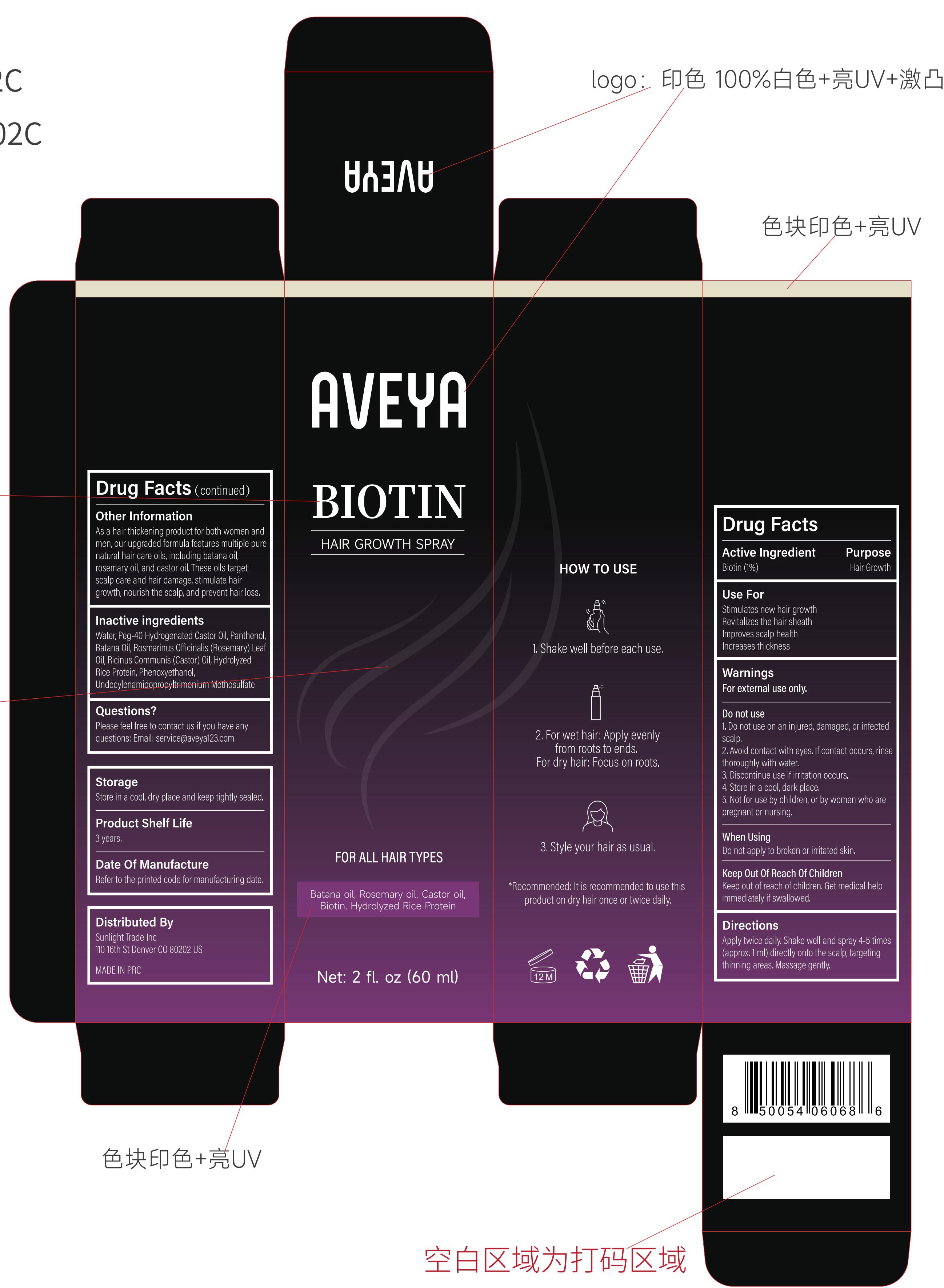 DRUG LABEL: AVEYA BIOTIN HAIR GROWTH
NDC: 83566-561 | Form: LIQUID
Manufacturer: Guangdong Aimu Biological Technology Co., Ltd
Category: otc | Type: HUMAN OTC DRUG LABEL
Date: 20251216

ACTIVE INGREDIENTS: BIOTIN 1 mg/100 mL
INACTIVE INGREDIENTS: PHENOXYETHANOL; ROSMARINUS OFFICINALIS (ROSEMARY) LEAF OIL; PANTHENOL; PEG-40 HYDROGENATED CASTOR OIL; UNDECYLENAMIDOPROPYLTRIMONIUM METHOSULFATE; WATER; JOJOBA OIL; HYDROLYZED RICE PROTEIN (ENZYMATIC; 2000 MW); RICINUS COMMUNIS (CASTOR) SEED OIL

AVEYA BIOTIN HAIR GROWTH

Active Ingredients

Biotin 1%

Purpose

Use ForStimulates new hair growth

Revitalizes the hair sheath

Improves scalp health

Increases thickness

Uses

DirectionsApply twice daily. Shakewell and spray 4-5 times(approx.1 ml) directly ontothe scalp, targeting thinningareas. Massage gently.

Warnings

For external use only.

Stop Use

Discontinue use if irritation occurs.

Do not use on an injured, damaged, or infectedscalp.

When Using

Avoid contact with eyes, lf contact occurs, rinsethoroughly with water.

Keep out of reach of children, Get medical helpimmediately if swallowed.

Dosage & administration

Recommended: it is recommended to use thisproduct on dry hair once or twice daily.

Inactive ingredients

Water 97.65%

Peg-40 Hydrogenated Castor 0il 0.15%

Panthenol 0.15%

Batana Oil 0.1%

Rosmarinus Officinalis (Rosemary) Leaf 0il 0.1%

Ricinus Communis (Castor) 0il 0.1%

Hydrolyzed Rice Protein 0.3%

Phenoxyethanol 0.35%

Undecylenamidopropyltnmonium Methosulfate 0.1%